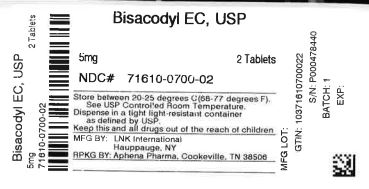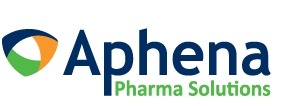 DRUG LABEL: Bisacodyl
NDC: 71610-700 | Form: TABLET, DELAYED RELEASE
Manufacturer: Aphena Pharma Solutions - Tennessee, LLC
Category: otc | Type: HUMAN OTC DRUG LABEL
Date: 20250110

ACTIVE INGREDIENTS: BISACODYL 5 mg/1 1
INACTIVE INGREDIENTS: ACACIA; AMMONIA; CALCIUM CARBONATE; CARNAUBA WAX; SILICON DIOXIDE; STARCH, CORN; D&C YELLOW NO. 10 ALUMINUM LAKE; FD&C YELLOW NO. 6; HYPROMELLOSE, UNSPECIFIED; FERROSOFERRIC OXIDE; ANHYDROUS LACTOSE; MAGNESIUM STEARATE; METHYLPARABEN; POLYDEXTROSE; POLYETHYLENE GLYCOL, UNSPECIFIED; POLYVINYL ACETATE PHTHALATE; POVIDONE, UNSPECIFIED; PROPYLENE GLYCOL; PROPYLPARABEN; SHELLAC; DIMETHICONE; WATER; SODIUM ALGINATE; SODIUM BENZOATE; SODIUM BICARBONATE; STEARIC ACID; SUCROSE; TALC; TITANIUM DIOXIDE; TRIACETIN; TRIETHYL CITRATE

Major 44-327

Active ingredient (in each tablet)

Bisacodyl USP, 5 mg

Purpose

Stimulant laxative

Uses

- for relief of occasional constipation and irregularity
- this product generally produces bowel movement in 6 to 12 hours

Warnings

Do not use

if you cannot swallow without chewing.

Ask a doctor before use if you have

- stomach pain, nausea or vomiting
- a sudden change in bowel habits that lasts more than 2 weeks

When using this product

- do not chew or crush tablet(s)
- do not use within 1 hour after taking an antacid or milk
- you may have stomach discomfort, faintness and cramps

Stop use and ask a doctor if

- you have rectal bleeding or fail to have a bowel movement after use of a laxative. These could be signs of a serious condition.
- you need to use a laxative for more than 1 week

If pregnant or breast-feeding,

ask a health professional before use.

Keep out of reach of children.

In case of overdose, get medical help or contact a Poison Control Center right away.

Directions

- take with a glass of water

adults and children 12 years and over | take 1 to 3 tablets in a single daily dose
children 6 to under 12 years | take 1 tablet in a single daily dose
children under 6 years | ask a doctor

Other information

- store at 25°C (77°F); excursions permitted between 15°-30°C (59°-86°F)
- avoid excessive humidity
- use by expiration date on package

Inactive ingredients

acacia, ammonium hydroxide, calcium carbonate, carnauba wax, colloidal anhydrous silica, corn starch, D&C yellow #10 aluminum lake, FD&C yellow #6 aluminum lake, hypromellose, iron oxide black, lactose anhydrous, magnesium stearate, methylparaben, polydextrose, polyethylene glycol, polyvinyl acetate phthalate, povidone, propylene glycol, propylparaben, shellac glaze, simethicone, sodium alginate, sodium benzoate, sodium bicarbonate, stearic acid, sucrose, talc, titanium dioxide, triacetin, triethyl citrate

Questions or comments?

(800)-616-2471

Repackaging Information

This drug product has been received by Aphena Pharma - TN in a manufacturer or distributor packaged configuration and repackaged in full compliance with all applicable cGMP regulations. The package configurations available from Aphena are listed below:

Count | 5 mg
2 | 71610-700-02
3 | 71610-700-03
4 | 71610-700-04
6 | 71610-700-06
8 | 71610-700-08
20 | 71610-700-20

Store between 20°-25°C (68°-77°F). See USP Controlled Room Temperature. Dispense in a tight light-resistant container as defined by USP. Keep this and all drugs out of the reach of children.

Repackaged by:
Cookeville, TN 38506
20230406JK

PRINCIPAL DISPLAY PANEL - 5 mg

NDC 71610-700 - Bisacodyl EC, USP 5 mg Tablets - Rx Only